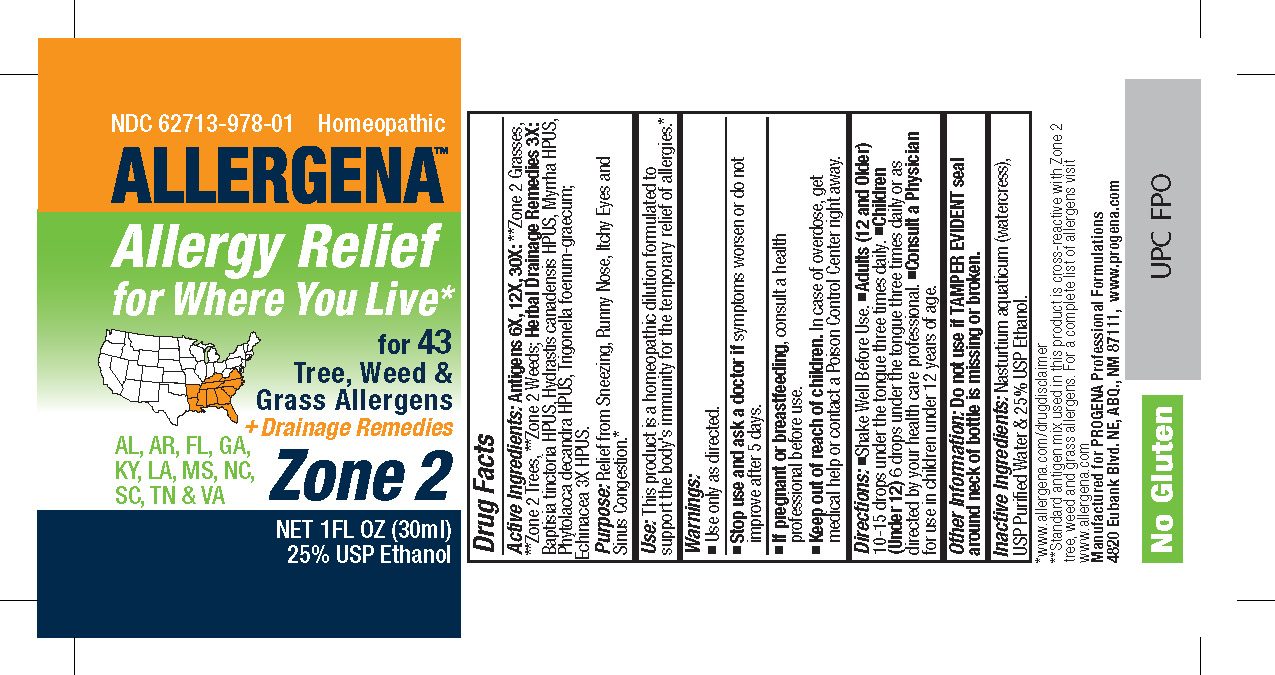 DRUG LABEL: Allergena Zone 2

NDC: 62713-978 | Form: LIQUID
Manufacturer: Meditrend, Inc. DBA Progena Professional Formulations
Category: homeopathic | Type: HUMAN OTC DRUG LABEL
Date: 20250130

ACTIVE INGREDIENTS: LOLIUM PERENNE POLLEN 30 [hp_X]/1 mL; ECHINACEA, UNSPECIFIED 3 [hp_X]/1 mL; BAPTISIA TINCTORIA ROOT 3 [hp_X]/1 mL; GOLDENSEAL 3 [hp_X]/1 mL; MYRRH 3 [hp_X]/1 mL; PHYTOLACCA AMERICANA ROOT 3 [hp_X]/1 mL; FENUGREEK LEAF 3 [hp_X]/1 mL; ACACIA POLLEN 30 [hp_X]/1 mL; FRAXINUS PENNSYLVANICA POLLEN 30 [hp_X]/1 mL; BETULA OCCIDENTALIS POLLEN 30 [hp_X]/1 mL; ACER NEGUNDO POLLEN 30 [hp_X]/1 mL; JUNIPERUS VIRGINIANA POLLEN 30 [hp_X]/1 mL; POPULUS DELTOIDES POLLEN 30 [hp_X]/1 mL; TAXODIUM DISTICHUM POLLEN 30 [hp_X]/1 mL; ULMUS AMERICANA POLLEN 30 [hp_X]/1 mL; CELTIS OCCIDENTALIS POLLEN 30 [hp_X]/1 mL; CARYA OVATA POLLEN 30 [hp_X]/1 mL; LIGUSTRUM VULGARE POLLEN 30 [hp_X]/1 mL; ACER SACCHARUM POLLEN 30 [hp_X]/1 mL; ACER RUBRUM POLLEN 30 [hp_X]/1 mL; MORUS RUBRA POLLEN 30 [hp_X]/1 mL; QUERCUS VIRGINIANA POLLEN 30 [hp_X]/1 mL; QUERCUS RUBRA POLLEN 30 [hp_X]/1 mL; QUERCUS ALBA POLLEN 30 [hp_X]/1 mL; CARYA ILLINOINENSIS POLLEN 30 [hp_X]/1 mL; PINUS STROBUS POLLEN 30 [hp_X]/1 mL; POPULUS ALBA POLLEN 30 [hp_X]/1 mL; LIQUIDAMBAR STYRACIFLUA POLLEN 30 [hp_X]/1 mL; PLATANUS OCCIDENTALIS POLLEN 30 [hp_X]/1 mL; JUGLANS NIGRA POLLEN 30 [hp_X]/1 mL; SALIX NIGRA POLLEN 30 [hp_X]/1 mL; BACCHARIS HALIMIFOLIA POLLEN 30 [hp_X]/1 mL; AMARANTHUS PALMERI POLLEN 30 [hp_X]/1 mL; XANTHIUM STRUMARIUM POLLEN 30 [hp_X]/1 mL; RUMEX CRISPUS POLLEN 30 [hp_X]/1 mL; CHENOPODIUM ALBUM POLLEN 30 [hp_X]/1 mL; IVA ANNUA POLLEN 30 [hp_X]/1 mL; ARTEMISIA VULGARIS POLLEN 30 [hp_X]/1 mL; URTICA DIOICA POLLEN 30 [hp_X]/1 mL; AMARANTHUS RETROFLEXUS POLLEN 30 [hp_X]/1 mL; PLANTAGO LANCEOLATA POLLEN 30 [hp_X]/1 mL; AMBROSIA TRIFIDA POLLEN 30 [hp_X]/1 mL; AMBROSIA ARTEMISIIFOLIA POLLEN 30 [hp_X]/1 mL; PASPALUM NOTATUM POLLEN 30 [hp_X]/1 mL; CYNODON DACTYLON POLLEN 30 [hp_X]/1 mL; POA PRATENSIS POLLEN 30 [hp_X]/1 mL; FESTUCA PRATENSIS POLLEN 30 [hp_X]/1 mL; SORGHUM HALEPENSE POLLEN 30 [hp_X]/1 mL; DACTYLIS GLOMERATA POLLEN 30 [hp_X]/1 mL; AGROSTIS GIGANTEA POLLEN 30 [hp_X]/1 mL
INACTIVE INGREDIENTS: WATER; ALCOHOL; NASTURTIUM OFFICINALE

Allergena Zone 2

ACTIVE INGREDIENT

Active Ingredients: Antigens 6X, 12X, 30X:**Zone 2 Grasses, **Zone 2 Trees, **Zone 2 Weeds; Herbal Drainage Remedies 3X:Baptisia tinctoria HPUS, Hydrastis canadensis HPUS, Myrrha HPUS, Phytolacca decandra HPUS, Trigonella foenum-graecum; Echinacea 3X HPUS.

PURPOSE

Purpose:Relief from Sneezing, Runny Nose, Itchy Eyes and Sinus Congestion.*

INDICATIONS AND USAGE

Use:This product is a Homeopathic Dilution formulated to support the body's immunity for the temporary relief of allergies.*

Keep Out of Reach of Children.In case of overdose, get medical help or contact a
Poison Control Center right away.

Warnings:

- Use Only as directed.
- Stop use and ask a doctorif symptoms worsen or do not improve after 5 days.
- If pregnant or breast-feeding, consult a health professional before use.

DOSAGE AND ADMINISTRATION

Directions:•Shake Well Before Use. • Adults (12 and Older)10-15 drops under the tongue three times daily. • Children (2-12) 6-10 drops under the tongue three times daily. • Infants (0-2)3-6 drops under the tongue three times daily or as directed by your health care professional.

Other Information: Do not use if TAMPER EVIDENT seal around neck of bottle is missing or broken.

INACTIVE INGREDIENT

Inactive Ingredients:Nasturtium aquaticum (watercress), USP Purified Water and 25% USP Ethanol.

PACKAGE LABEL

*www.allergena.com/drugdisclaimer
**Standard antigen mix used in this product is cross-reactive with Zone 2 Tree, Weed, and Grass allergens. For a complete list of allergens visit
www.allergena.com

Manufactured for PROGENA Professional Formulations
4820 Eubank Blvd. NE, ABQ, NM 87111, www.progena.com